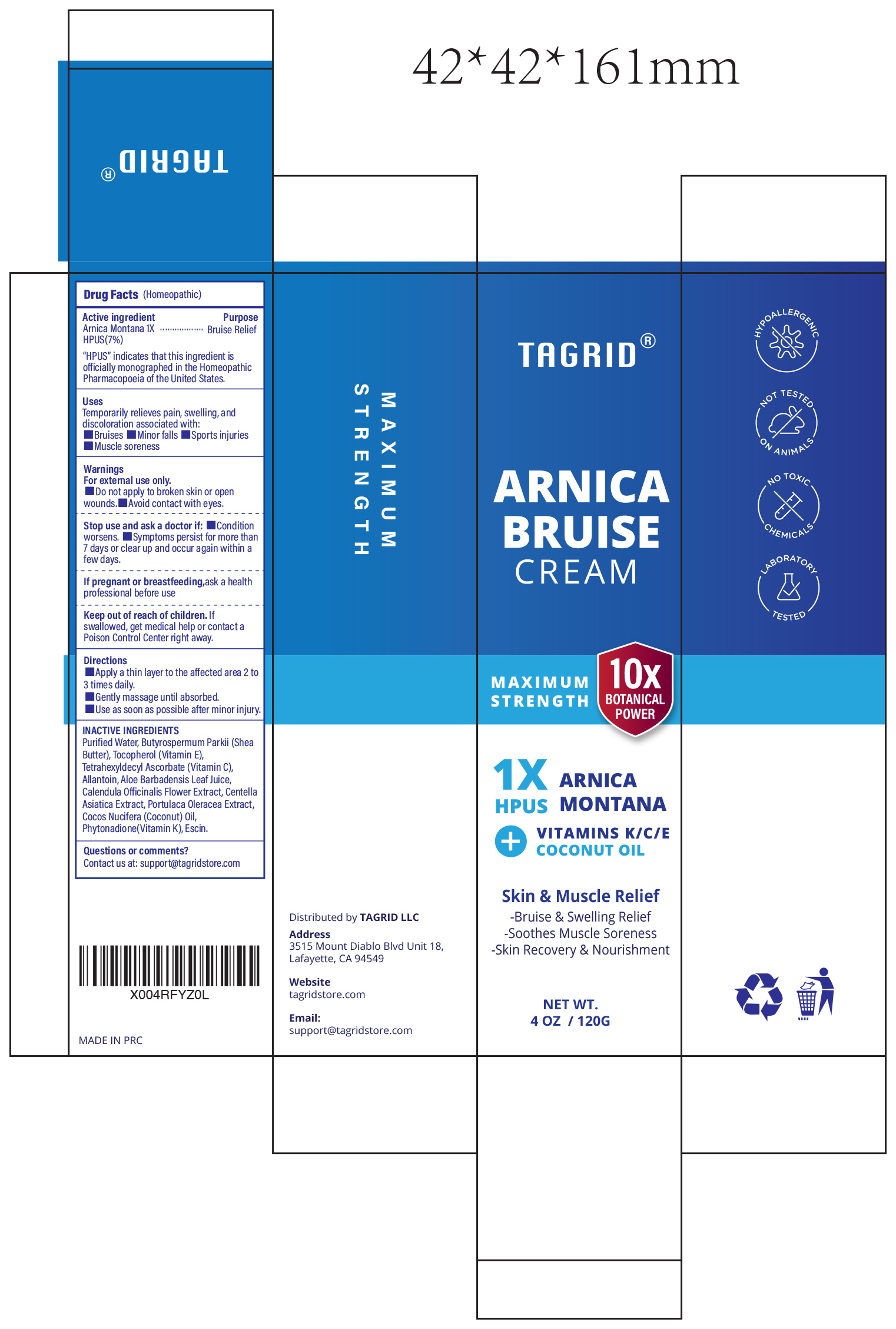 DRUG LABEL: Tagrid Arnica Bruise Arnica Montana 1X HPUS (7%)
NDC: 85384-0015 | Form: CREAM
Manufacturer: TAGRID LLC
Category: homeopathic | Type: HUMAN OTC DRUG LABEL
Date: 20250719

ACTIVE INGREDIENTS: Arnica Montana 7 mg/100 g
INACTIVE INGREDIENTS: WATER; SHEA BUTTER; TOCOPHEROL; TETRAHEXYLDECYL ASCORBATE; ALLANTOIN; ALOE BARBADENSIS LEAF JUICE; CALENDULA OFFICINALIS FLOWER; CENTELLA ASIATICA TRITERPENOIDS; PURSLANE; COCONUT OIL; PHYTONADIONE; ESCIN

Active ingredient:

1. Arnica Montana 1X HPUS (7%)

PURPOSE

Purpuse:Bruise Relief.

"HPUS" indicates that this ingredient is officially monographed in the Homeopathic Pharmacopoeia of the United States.

INDICATIONS AND USAGE

Uses: Temporarily relieves pain, swelling, and discoloration associated with:

1. Bruises
2. Minor falls
3. Sports injuries
4. Muscle soreness

WARNINGS

For external use only

DO NOT USE

Do not apply to broken skin or open wounds. Avoid contact with eyes.

When using this product

Avoid contact with eyes.

Stop use and ask a doctor if

- Condition worsens
- Symptoms persist for more than 7 days or clear up and occur again within a few days.

If pregnant or breast-feeding

Ask a health professional before use

Keep out of reach of children.

If swallowed, get medical help or contact a Poison Control Center right away.

Directions:

- Apply a thin layer to the affected area 2 to 3 times daily.
- Gently massage until absorbed.
- Use as soon as possible after minor injury.

Inactive ingredients:

- Purified Water
- Butyrospermum Parkii (Shea Butter)
- Tocopherol (Vitamin E)
- Tetrahexyldecyl Ascorbate (Vitamin C)
- Allantoin
- Aloe Barbadensis Leaf Juice
- Calendula Officinalis Flower Extract
- Centella Asiatica Extract
- Portulaca Oleracea Extract
- Cocos Nucifera (Coconut) Oil
- Phytonadione (Vitamin K)
- Escin

Questions or comments?

Contact us at support@tagridstore.com